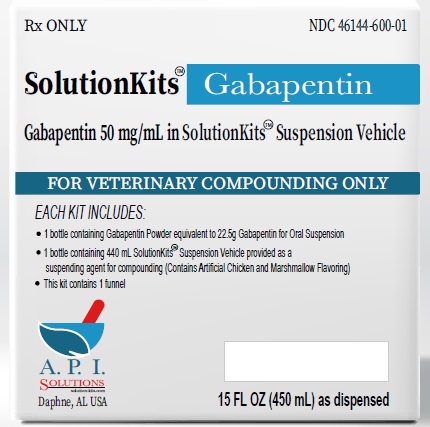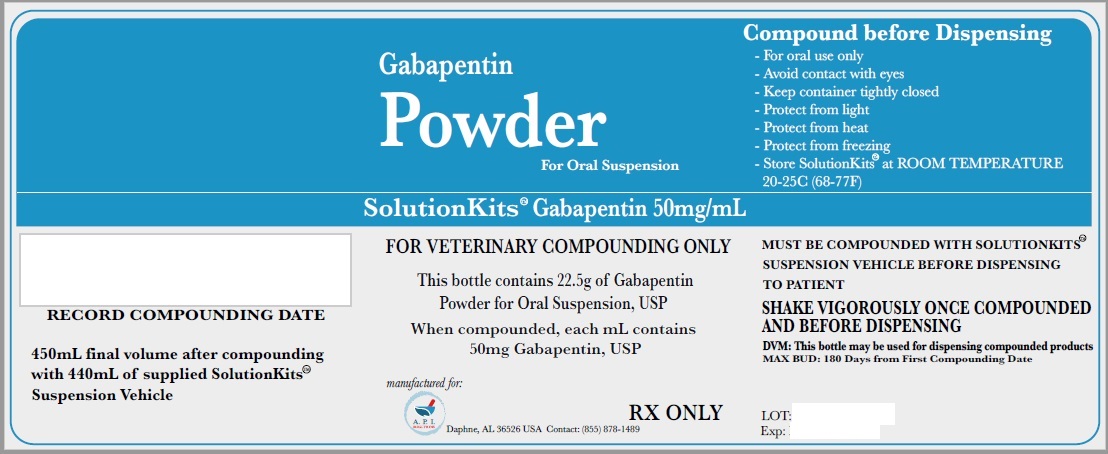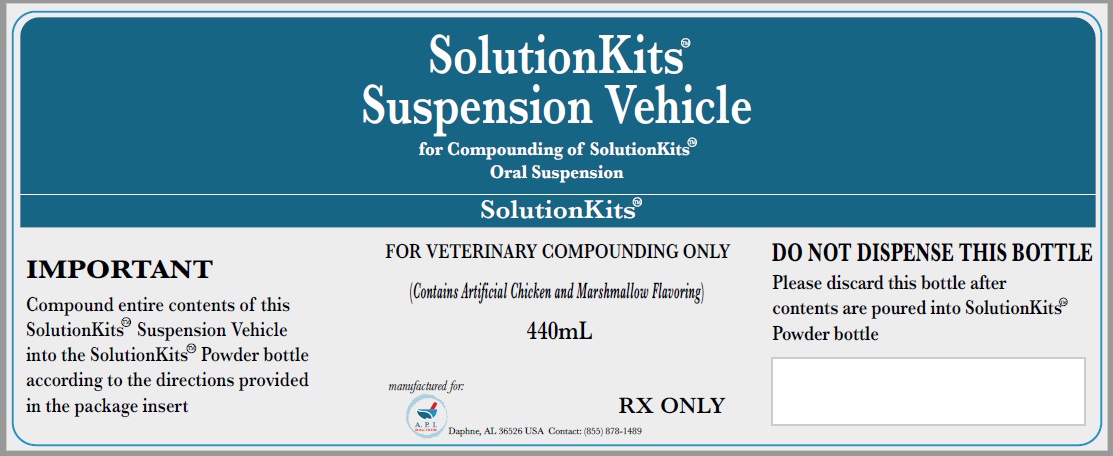 DRUG LABEL: SolutitionKits
NDC: 46144-600 | Form: KIT | Route: NOT APPLICABLE
Manufacturer: API Solutions
Category: other | Type: BULK INGREDIENT - ANIMAL DRUG
Date: 20250323

ACTIVE INGREDIENTS: GABAPENTIN 1 g/1 g
INACTIVE INGREDIENTS: MEDIUM-CHAIN TRIGLYCERIDES; AMMONIUM GLYCYRRHIZATE; COCONUT OIL; BUTYLATED HYDROXYANISOLE; POLYGLYCERYL-3 OLEATE; SILICON DIOXIDE

SolutionsKits Gabapentin USP

SolutionKits™Gabapentin

Gabapentin 50 mg/mL in SolutionKits™ Suspension Vehicle

FOR VETERINARY COMPOUNDING ONLY

Each kit includes:

1 bottle containing Gabapentin Powder equivalent to 22.5g Gabapentin for Oral Suspension

1 bottle containing 440 mL SolutionKits™ Suspension Vehicle provided as a suspending agent for compounding (Contains Artificial Chicken and Marshmallow Flavoring)

This kit contains 1 funnel

A.P.I.

Solutions

Daphne, AL USA

15 FL OZ (450 mL) as dispensed